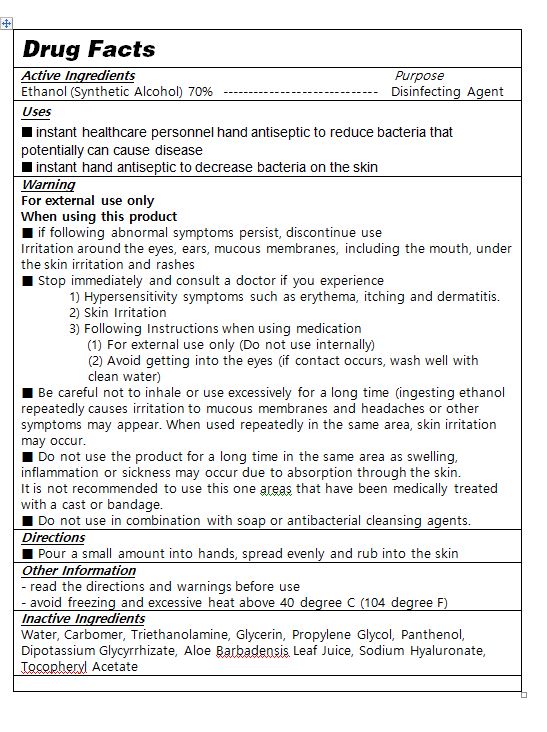 DRUG LABEL: PERFUME ON HAND SANITIZER gel BABYPOWDER
NDC: 77600-0002 | Form: GEL
Manufacturer: ASCENT LAB
Category: otc | Type: HUMAN OTC DRUG LABEL
Date: 20200512

ACTIVE INGREDIENTS: ALCOHOL 70 mL/100 mL
INACTIVE INGREDIENTS: TROLAMINE; WATER; ALOE VERA LEAF; CARBOMER 940; GLYCERIN

Drug Facts

ACTIVE INGREDIENT

alcohol

PURPOSE

sterilization of hands, skin and so on

KEEP OUT OF REACH OF THE CHILDREN

INDICATIONS AND USAGE

take appropriate amount on the hand, rub and dry well

WARNINGS

■ Flammable. Keep away from fire or flame.

■ For external use only.

■ Do not use in eyes.

■ lf swallowed, get medical help promptly.

■ Stop use, ask doctor lf irritation occurs.

■ Keep out of reach of children.

DOSAGE AND ADMINISTRATION

for external use only

INACTIVE INGREDIENT

Water, Carbomer, Triethanolamine, Glycerin, Propylene Glycol, Panthenol, Dipotassium Glycyrrhizate, Aloe Barbadensis Leaf Juice, Sodium Hyaluronate, Tocopheryl Acetate